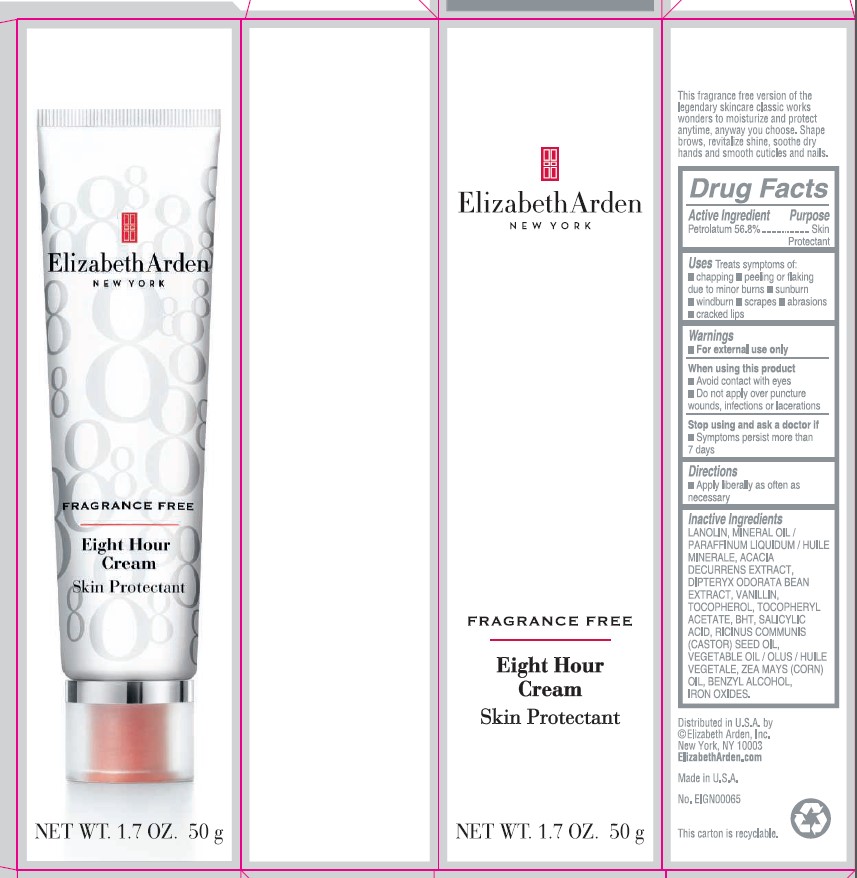 DRUG LABEL: EIGHT HOUR SKIN FRAGRANCE FREE
NDC: 10967-673 | Form: CREAM
Manufacturer: REVLON
Category: otc | Type: HUMAN OTC DRUG LABEL
Date: 20250801

ACTIVE INGREDIENTS: PETROLATUM 56.8 mg/1 g
INACTIVE INGREDIENTS: ACACIA DECURRENS WHOLE; MINERAL OIL; BUTYLATED HYDROXYTOLUENE; SALICYLIC ACID; FERRIC OXIDE RED; FERRIC OXIDE YELLOW; CORN OIL; DIPTERYX ODORATA SEED; VANILLIN; CASTOR OIL; BENZYL ALCOHOL; LANOLIN; TOCOPHEROL; .ALPHA.-TOCOPHEROL ACETATE

ELIZABETH ARDEN EIGHT HOUR CREAM SKIN PROTECTANT FRAGRANCE FREE

ACTIVE INGREDIENT

PETROLATUM 56.8%

INACTIVE INGREDIENTS

LANOLIN, MINERAL OIL/PARAFFINUM LIQUIDUM/HUILE MINÉRALE, ACACIA DECURRENS EXTRACT, DIPTERYX ODORATA BEAN EXTRACT, VANILLIN, TOCOPHEROL, TOCOPHERYL ACETATE, BHT, SALICYLIC ACID, RICINUS COMMUNIS (CASTOR) SEED OIL, VEGETABLE OIL/OLUS/HUILE VÉGÉTALE, ZEA MAYS (CORN) OIL, BENZYL ALCOHOL, IRON OXIDES

USES

Treats symptoms of:

- chapping
- peeling or flaking due to minor burns
- sunburn
- windburn
- scrapes
- abrasions
- cracked lips

WARNINGS

- For external use only

When using this product

- Avoid contact with eyes
- Do not apply over puncture wounds, infections or lacerations

Stop using and ask a doctor if

- Symptoms persist more than 7 days

DIRECTIONS

Apply liberally as often as necessary

DOSAGE AND ADMINISTRATION

Apply liberally as often as necessary

WARNINGS

For external use only

USES

Treats symptoms of:

- chapping
- peeling or flaking due to minor burns
- sunburn
- windburn
- scrapes
- abrasions
- cracked lips

KEEP OUT OF REACH OF CHILDREN

NA

PURPOSE

Skin Protectant